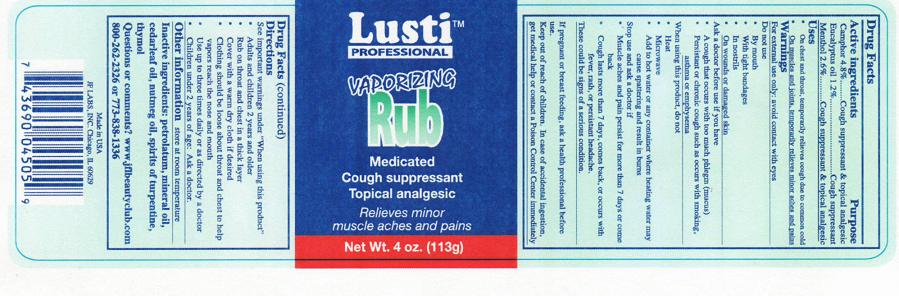 DRUG LABEL: Lusti Profesional Vaporizing Rub 
NDC: 49681-012 | Form: OINTMENT
Manufacturer: New Life Products, Inc.
Category: otc | Type: HUMAN OTC DRUG LABEL
Date: 20230202

ACTIVE INGREDIENTS: CAMPHOR (SYNTHETIC) .048 g/1 g; EUCALYPTUS OIL .012 g/1 g; MENTHOL, UNSPECIFIED FORM .026 g/1 g
INACTIVE INGREDIENTS: PETROLATUM; MINERAL OIL; CEDAR LEAF OIL; NUTMEG OIL; TURPENTINE; THYMOL

Lusti Professional Vaporizing Rub

OTC - ACTIVE INGREDIENT SECTION

Camphor 4.8% Eucalyptus Oil 1.2% Menthol 2.6%

OTC - PURPOSE SECTION

Cough suppressant & topical analgesic

Uses

- On chest an throat, temporarily relieves cough due to common cold
- On muscles and joints, temporarily relieves minor aches and pains

WARNINGS SECTION

For external use only; avoid contact with eyes

OTC - DO NOT USE SECTION

By mouth With tight bandages In nostrils On wounds or damaged skin

OTC - ASK DOCTOR SECTION

Before use if you have a cough that occurs with too much phlegm (mucus) persistant or chronic cough such as occurs with smoking, asthma or emphysema

OTC - WHEN USING SECTION

Do not heat, microwave, add to hot water or any container where heating water may cause spattering and result in burns

OTC - STOP USE SECTION

Stop use and ask a doctor if muscle aches and pain persist for more than 7 days or come back. Cough lasts more than 7 days or comes back or occurs with fever, rash, or persistant headache. These could be signs of a serious condition.

OTC - PREGNANCY OR BREAST FEEDING SECTION

If pregnant or breast feeding, ask a health professional before use.

OTC - KEEP OUT OF REACH OF CHILDREN SECTION

Keep out of reach of children. In case of accidental ingestion, get medical help or contact a Poison Control Center Immediately.

OTC - QUESTIONS SECTION

Questions or comments? www.jflbeautyclub.com 800-262-2326 773-838-1336

DIRECTIONS

See important warnings under "When using this product". Adults and children 2 years and older, rub on throat and chest in a thick layer. Cover with a warm dry cloth if desired. Clothing should be loose about throat and chest to help vapors reach the nose and mouth. Use up to three times daily or as directed by a doctor. Children under 2 years of age: Ask a doctor.

INACTIVE INGREDIENT SECTION

Petrolatum, Mineral Oil, Cedarleaf Oil, Nutmeg Oil, Spirits of Turpentine, Thymol

STORAGE AND HANDLING SECTION

Store at room temperature

PACKAGE LABEL.

Lusti Professional Vaporizing Rub
Medicated Cough suppressant Topical analgesic
Relieves minor muscle aches and pains
Net Wt. 4 Oz. (113g)

Drug Facts

Active ingredients | Purpose
Camphor 4.8% | Cough suppressant & topical analgesic
Eucalyptus oil 1.2% | Cough suppressant
Menthol 2.6% | Cough suppressant & topical analgesic

Uses

- On chest an throat, temporarily relieves cough due to common cold
- On muscles and joints, temporarily relieves minor aches and pains

Warnings
For external use only; avoid contact with eyes
Do not use

- By mouth
- With tight bandages
- In nostrils
- On wounds or damaged skin

Ask a doctor before use if you have

- A cough that occurs with too much phlegm (mucus)
- Persistant or chronic cough such as occurs with smoking, asthma or emphysema

When using this product, do not

- Heat
- Microwave
- Add to hot water or any container where heating water may cause spattering and result in burns

Stop use an ask a doctor if

- Muscle aches and pain persist for more than 7 days or come back
- Cough lasts more than 7 days, comes back, or occurs with fever, rash, or persistant headache.

These could be signs of a serious condition.
If pregnant or breast feeding, ask a health professional before use.
Keep out of reach of children. In case of accidental ingestion, get medical help or contact a Poison Control Center immediately

See important warnings under "When using this product"

- Adults and children 2 years and older
- Rub on throat and chest in a thick layer
- Cover with a warm dry cloth if desired
- Clothing should be loose about throat and chest to help vapors reach the nose and mouth
- Use up to three times daily or as directed by a doctor
- Children under 2 years of age: Ask a doctor.

Other information store at room temperature

Inactive ingredients: petrolatum, mineral oil, cedarleaf oil, nutmeg oil, spirits of turpentine, thymol

Questions or comments? www.jflbeautyclub.com
800-262-2326 or 773-838-1336

Made in USA
JF LABS, INC. Chicago, Illinois 60629